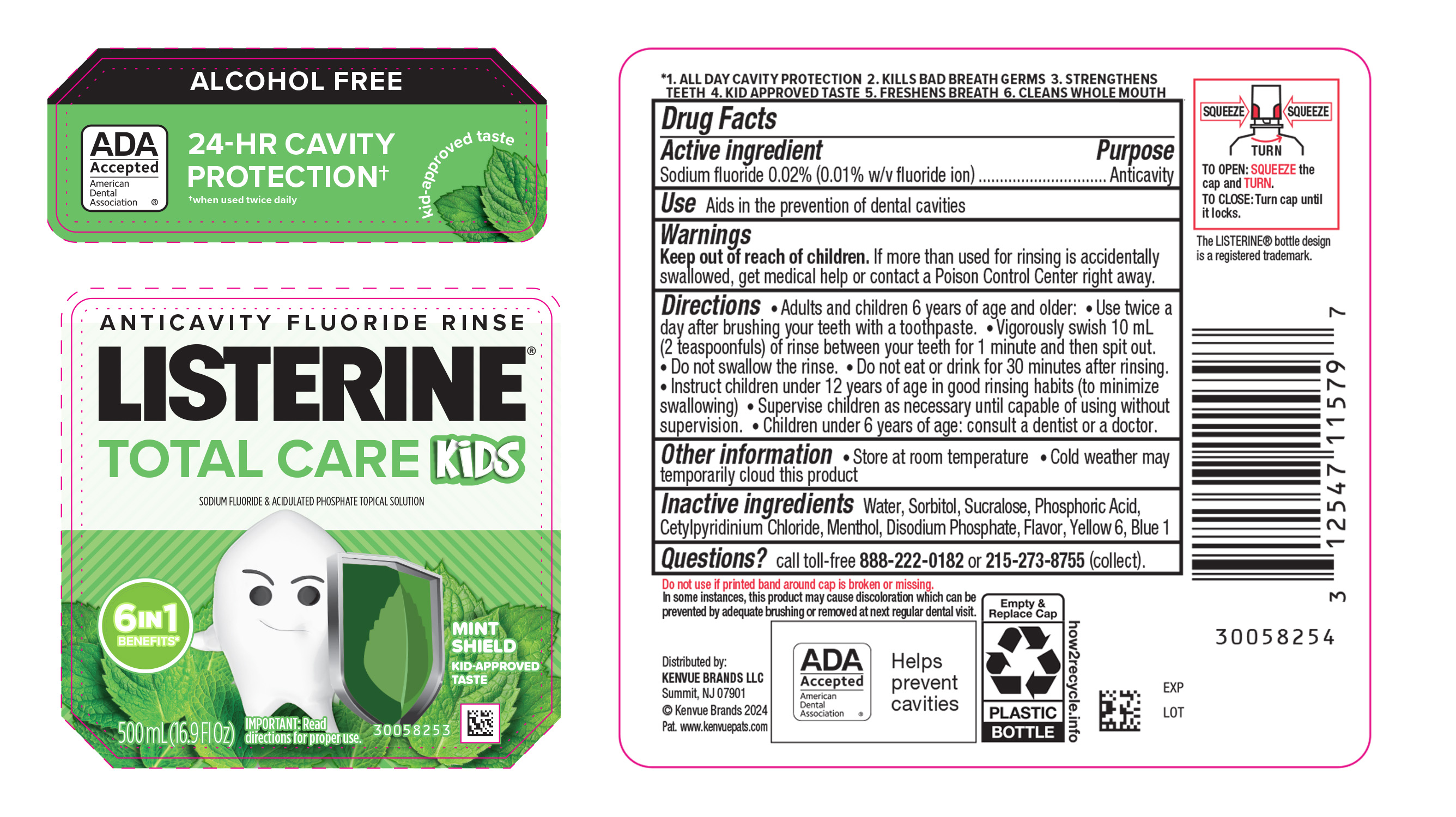 DRUG LABEL: Listerine Total Care Kids Anticavity Fluoride Rinse  Mint Shield
NDC: 69968-0902 | Form: MOUTHWASH
Manufacturer: Kenvue Brands LLC
Category: otc | Type: HUMAN OTC DRUG LABEL
Date: 20250213

ACTIVE INGREDIENTS: SODIUM FLUORIDE 0.1 mg/1 mL
INACTIVE INGREDIENTS: WATER; SORBITOL; SUCRALOSE; PHOSPHORIC ACID; CETYLPYRIDINIUM CHLORIDE; MENTHOL, UNSPECIFIED FORM; SODIUM PHOSPHATE, DIBASIC, ANHYDROUS; FD&C YELLOW NO. 6; FD&C BLUE NO. 1

Listerine Total Care Kids Anticavity Fluoride Rinse Mint Shield

Drug Facts

Active ingredient

Sodium fluoride 0.02% (0.01% w/v fluoride ion)

Purpose

Anticavity

Use

Aids in the prevention of dental cavities

Warnings

Keep out of reach of children. If more than used for rinsing is accidentally swallowed, get medical help or contact a Poison Control Center right away.

Directions

- Adults and children 6 years of age and older:
  - Use twice a day after brushing your teeth with a toothpaste
  - Vigorously swish 10 mL (2 teaspoonfuls) of rinse between your teeth for 1 minute and then spit out
  - Do not swallow the rinse
  - Do not eat or drink for 30 minutes after rinsing
  - Instruct children under 12 years of age in good rinsing habits (to minimize swallowing)
  - Supervise children as necessary until capable of using without supervision
- Children under 6 years of age: consult a dentist or a doctor

Other information

- Store at room temperature
- Cold weather may temporarily cloud this product

Inactive ingredients

Water, Sorbitol, Sucralose, Phosphoric Acid, Cetylpyridinium Chloride, Menthol, Disodium Phosphate, Flavor, Yellow 6, Blue 1

Questions?

call toll-free 888-222-0182 or 215-273-8755 (collect).

Distributed by:
Kenvue Brands LLC
Summit, NJ 07901

PRINCIPAL DISPLAY PANEL - 500 mL Bottle Label

ALCOHOL FREE

ADA

Accepted

American

Dental

Association ®

24-HR CAVITY

PROTECTION†

†when used twice daily

kid-approved taste

ANTICAVITY FLUORIDE RINSE

LISTERINE®

TOTAL CARE KiDS

SODIUM FLUORIDE & ACIDULATED PHOSPAHTE TOPICAL SOLUTION

6IN1

BENEFITS*

MINT

SHEILD

KID-APPROVED

TASTE

500 mL (16.9Fl Oz)

IMPORTANT: Read

directions for proper use.